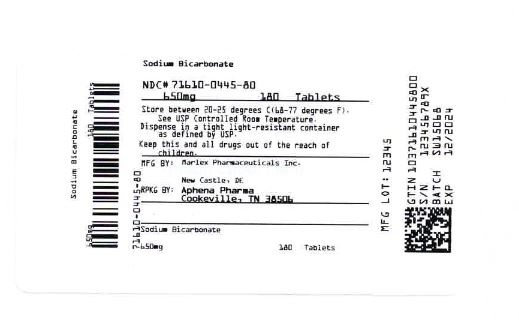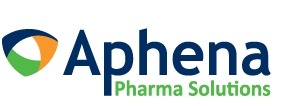 DRUG LABEL: Sodium Bicarbonate
NDC: 71610-445 | Form: TABLET
Manufacturer: Aphena Pharma Solutions - Tennessee, LLC
Category: otc | Type: HUMAN OTC DRUG LABEL
Date: 20200723

ACTIVE INGREDIENTS: SODIUM BICARBONATE 650 mg/1 1
INACTIVE INGREDIENTS: STARCH, CORN; MINERAL OIL

Sodium Bicarbonate Tablets

SODIUM BICARBONATE - sodium bicarbonate tablet

Marlex Pharmaceuticals, Inc.

Disclaimer: Most OTC drugs are not reviewed and approved by FDA; however, they may be marketed if they comply with applicable regulations and policies. FDA has not evaluated whether this product complies.

----------

Sodium Bicarbonate

Active ingredient (in each tablet)

Sodium bicarbonate 10 gr (650 mg)

Sodium bicarbonate 5gr (325 mg)

Purpose

Antacid

Uses

Relieves

- acid indigestion heartburn
- sour stomach
- upset stomach associated with these symptoms

Warnings

Ask a doctor before use if you have

a sodium restricted diet

Ask a doctor or pharmacist before use if you are

taking a prescription drug. Antacids may interact with certain prescription drugs.

Stop use and ask a doctor if

symptoms last more than 2 weeks

If pregnant or breast-feeding,

ask a health professional before use.

Directions

- do not use the maximum dosage for more than 2 weeks
- dissolve tablets completely in water prior to use

325mg,

- adults 60 years of age and over: 2-8 tablets every 4 hours, not more than 24 tablets in 24 hours
- adults under 60 years of age: 2-8 tablets every 4 hours, not more than 48 tablets in 24 hours

650mg,

- adults 60 years of age and over: 1-2 tablets every 4 hours, not more than 12 tablets in 24 hours
- adults under 60 years of age: 1-4 tablets every 4 hours, not more than 24 tablets in 24 hours

Other information

- each tablet contains: sodium 89mg (325mg)
- store at room temperature 15°-30°C (59°-86°F) in well-closed containers as defined in the USP

sodium 178 mg (650mg)

Inactive ingredients

Pregelatinized starch, NF and mineral oil, USP

Questions or comments?

Call toll free 1-888-266-8818

TAMPER EVIDENT: DO NOT USE IF IMPRINTED SAFETY SEAL UNDER CAP IS BROKEN OR MISSING

Repackaging Information

Please reference the How Supplied section listed above for a description of individual tablets. This drug product has been received by Aphena Pharma - TN in a manufacturer or distributor packaged configuration and repackaged in full compliance with all applicable cGMP regulations. The package configurations available from Aphena are listed below:

Count | 650 mg
60 | 71610-445-53
90 | 71610-445-60
180 | 71610-445-80

Store between 20°-25°C (68°-77°F). See USP Controlled Room Temperature. Dispense in a tight light-resistant container as defined by USP. Keep this and all drugs out of the reach of children.

Repackaged by:
Cookeville, TN 38506
20200723JH

PRINCIPAL DISPLAY PANEL - 650 mg

NDC 71610-445 - Sodium Bicarbonate 650 mg Tablets